DRUG LABEL: Killa Acne Extra Strength
NDC: 81746-420 | Form: PATCH
Manufacturer: Zitsticka, Inc.
Category: otc | Type: HUMAN OTC DRUG LABEL
Date: 20230616

ACTIVE INGREDIENTS: SALICYLIC ACID 0.0125 mg/0.6216 mg
INACTIVE INGREDIENTS: OLIGOPEPTIDE-10; NIACINAMIDE; GLYCOLIC ACID; 4-BUTYLRESORCINOL; HYALURONATE SODIUM; MADECASSOSIDE; PHYTOSPHINGOSINE HYDROCHLORIDE

Active Ingredients

Salicylic Acid 2%

Purpose

Acne Treatment

Ask a doctor

If irritation becomes severe

When using this product

Skin irritation and dryness may occur if you use another topical acne medication at the same time or immediately following. If irritation occurs, only use one topical acne medication at a time unless directed by a doctor.

Keep out of reach of children

If swallowed, get medical help or contact a Posion Control Center right away.

NA

Warnings

For extrernal use only

Inactive Ingredients

Sodium Hyaluronate, Phytosphingosine HCL, Niacinamide, Oligopeptide-10, Glycolic Acid, Madecassoside, 4-Butylresorcinol.

Patch: Hydrocolloid

Uses

- For the management of acne.
- Penetrates pores to eliminate most blemishes